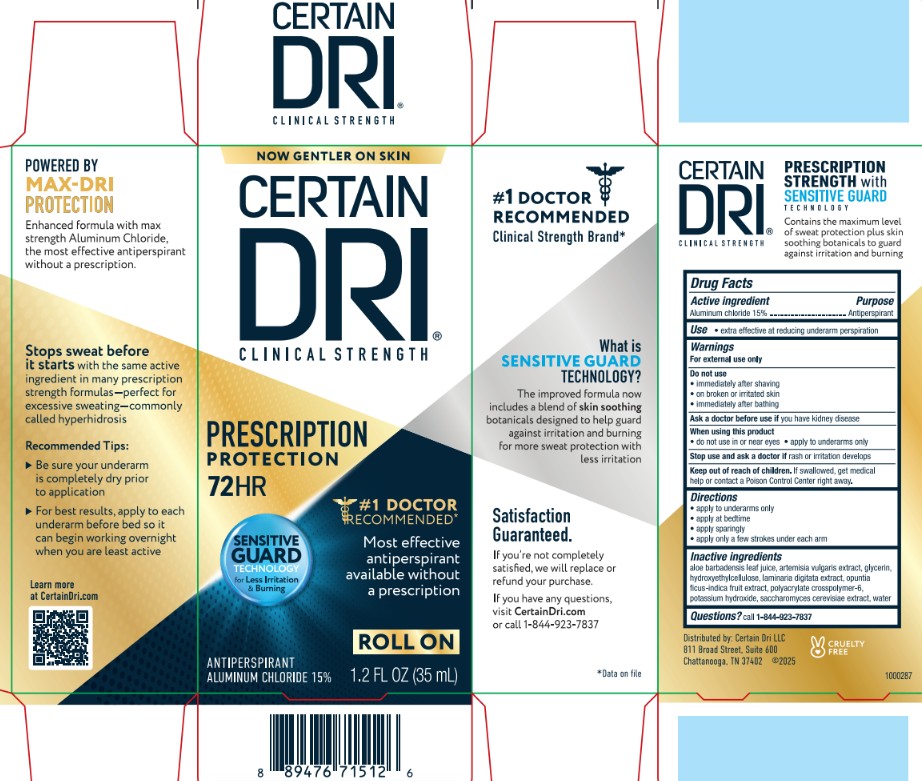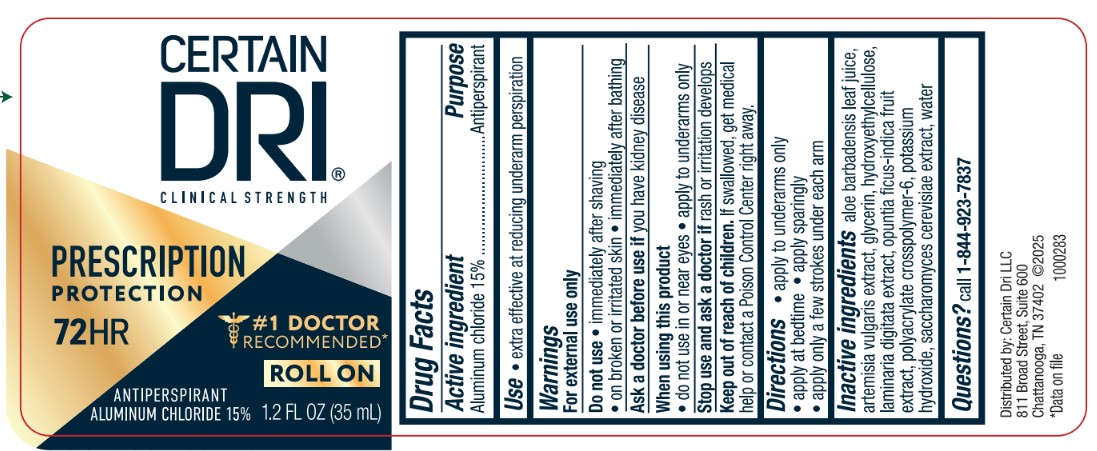 DRUG LABEL: Certain Dri Clinical Strength Prescription Protection Rollon
NDC: 69693-734 | Form: LIQUID
Manufacturer: Clarion Brands LLC
Category: otc | Type: HUMAN OTC DRUG LABEL
Date: 20251223

ACTIVE INGREDIENTS: ALUMINUM CHLORIDE 15 g/100 mL
INACTIVE INGREDIENTS: HYDROXYETHYLCELLULOSE; WATER; ALOE BARBADENSIS LEAF JUICE; OPUNTIA FICUS-INDICA FRUIT JUICE; ARTEMISIA VULGARIS ROOT; GLYCERIN; SACCHAROMYCES CEREVISIAE; POTASSIUM HYDROXIDE; LAMINARIA DIGITATA; POLYACRYLATE CROSSPOLYMER-6

ACTIVE INGREDIENT

Aluminum chloride 15%

PURPOSE

Antiperspirant

INDICATIONS AND USAGE

- extra effective at reducing underarm perspiration

WARNINGS

For external use only

Ask a doctor before use if you have kidney disease

DO NOT USE

- immediately after shaving
- on broken or irritated skin
- immediately after bathing

- do not use in or near eyes
- apply to underarms only

Stop use and ask a doctor if rash or irritation develops

Keep out of reach of children. If swallowed, get medical help or contact a Poison Control Center right away.

DOSAGE AND ADMINISTRATION

- apply to underarms only
- apply at bedtime
- apply sparingly
- apply only a few strokes under each arm

INACTIVE INGREDIENT

aloe barbadensis leaf juice, artemisia vulgaris extract, glycerin, hydroxyethylcellulose, laminaria digitata extract, opuntia ficus-indica fruit extract, polyacrylate crosspolymer-6, potassium hydroxide, saccharomyces cerevisiae extract, water

Questions? call 1-844-923-7837

PACKAGE LABEL

NOW GENTLER ON SKIN

CERTAIN DRI®

CLINICAL STRENGTH

PRESCRIPTION PROTECTION

72 HR

SENSITIVE GUARD TECHNOLOGY for Less Irritation & Burning

#1 Doctor Recommended

Most effective antiperspirant available without a prescription

ROLLON

ANTIPERSPIRANT ALUMINUM CHLORIDE 15%

1.2 FL OZ (35 mL)

#1 DOCTOR RECOMMENDED

Clinical Strength Brand*

What is SENSITIVE GUARD TECHNOLOGY?

The improved formula now includes a blend of skin soothing botanicals designed to help guard against irritation and burning for more sweat protection with less irritation

Satisfaction Guaranteed.

If you're not completely satisfied, we will replace or refund your purchase.

If you have any questions, visit CertainDri.com or call 1-844-823-7837

*Data on file

POWERED BY MAX-DRI PROTECTION

Enhanced formula with max strength Aluminum Chloride, the most effective antiperspirant without a prescription.

Stops sweat before it starts with the same active ingredient in many prescription strength formulas-perfect for excessive sweating-commonly called hyperhidrosis

Recommended Tips:

- Be sure your underarm is completely dry prior to application
- For best results, apply to each underarm before bed so it can begin working overnight when you are least active

Learn more at CertainDri.com

CERTAIN DRI® CLINICAL STRENGTH PRESCRIPTION STRENGTH with SENSITIVE GUARD TECHNOLOGY

Contains the maximum level of sweat protection plus skin soothing botanicals to guard against irritation and burning

CERTAIN DRI®

CLINICAL STRENGTH

PRESCRIPTION PROTECTION

72 HR

#1 Doctor Recommended*

ROLLON

ANTIPERSPIRANT ALUMINUM CHLORIDE 15%

1.2 FL OZ (35 mL)

Distributed by: Certain Dri LLC

811 Broad Street, Suite 600

Chattanooga, TN 37402 ©2025

*Data on file 1000283